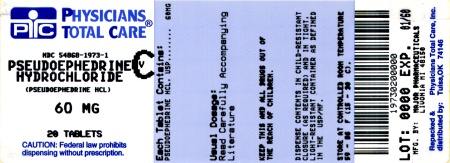 DRUG LABEL: Pseudoephedrine Hydrochloride
NDC: 54868-1973 | Form: TABLET, FILM COATED
Manufacturer: Physicians Total Care, Inc.
Category: otc | Type: HUMAN OTC DRUG LABEL
Date: 20120124

ACTIVE INGREDIENTS: PSEUDOEPHEDRINE HYDROCHLORIDE 60 mg/1 1
INACTIVE INGREDIENTS: HYPROMELLOSES; LACTOSE; MAGNESIUM STEARATE; POLYETHYLENE GLYCOL; SILICON DIOXIDE; STEARIC ACID; CELLULOSE, MICROCRYSTALLINE

SudoGest
Nasal Decongestant

Active ingredient

Pseudoephedrine HCl 60 mg

Purpose

Nasal decongestant

Uses

- temporarily relieves nasal congestion due to the common cold, hay fever or other upper respiratory allergies
- temporarily relieves sinus congestion and pressure

Warnings

Do not use

- if you are now taking a prescription monoamine oxidase inhibitor (MAOI) (certain drugs for depression, psychiatric or emotional conditions, or Parkinson's disease), or for 2 weeks after stopping the MAOI drug. If you do not know if your prescription drug contains an MAOI, ask a doctor or pharmacist before taking this product.

Ask a doctor before use if you have

- diabetes
- thyroid disease
- heart disease
- high blood pressure
- trouble urinating due to enlargement of the prostate gland

When using this product

- do not exceed recommended dose

Stop use and ask a doctor if

- nervousness, dizziness, or sleeplessness occur
- symptoms do not improve within 7 days or occur with fever

If pregrant or breast-feeding,

ask a health professional before use.

Keep out of reach of children.

In case of overdose, get medical help or contact a Poison Control Center right away.

Directions

- adults and children 12 years and older: take 1 tablet every 4 to 6 hours. Do not take more than 4 tablets in 24 hours.
- children under 12 years of age: do not use

Other information

- store at controlled room temperature 15˚-30˚C (59˚-86˚F)
- see end flap for expiration date and lot number

Inactive ingredients

corn starch, hypromellose, lactose, magnesium stearate, microcrystalline cellulose, polyethylene glycol, silicon dioxide, stearic acid

Principal display panel

The product packaging shown below represents a sample of that currently in use. Additional packaging may also be available

FOR PHARMACY USE ONLY.

NOT FOR RETAIL SALE.

NDC 54868-1973-1

Pseudoephedrine Hydrochloride 60 mg

NASAL DECONGESTANT 60 mg

Relieves Nasal and Sinus Congestion due to Colds or Hay Fever

Without Drowsiness

TAMPER EVIDENT: DO NOT USE IF IMPRINTED SAFETY SEAL UNDER CAP IS BROKEN OR MISSING

50844 Rev. 0807L11302

Distributed by Major Pharmaceuticals

31778 Enterprise Drive

Livonia, MI 48150 USA M-17

Rev. 10/10 Re-order No. 700324

Relabeing and Repackaging by:
Physicians Total Care, Inc.
Tulsa, Oklahoma 74146